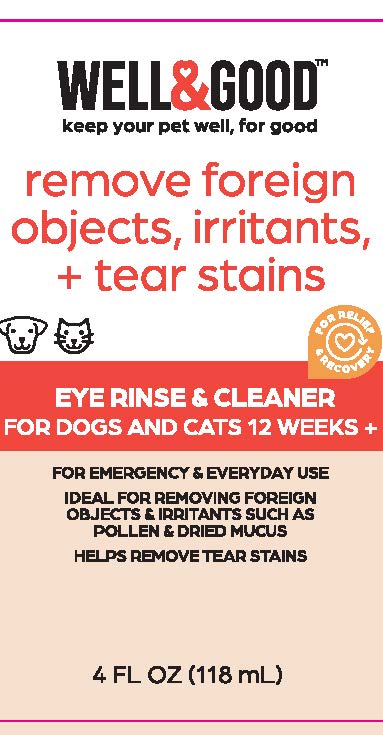 DRUG LABEL: Well and Good Eye Rinse and Cleaner
NDC: 77720-028 | Form: LIQUID
Manufacturer: Skaffles Group Limited Liability Company
Category: animal | Type: OTC ANIMAL DRUG LABEL
Date: 20220915

ACTIVE INGREDIENTS: WATER 106.3 mL/118 mL
INACTIVE INGREDIENTS: BORIC ACID; SODIUM BORATE; SODIUM CHLORIDE; SORBIC ACID; EDETATE DISODIUM

Eye Rinse and Cleaner

Active ingredients

Purified Water.

DESCRIPTION

The WELL & GOOD EYE
RINSE & CLEANER is a
soothing eye solution that is
formulated to cleanse and
relieve irritotion in sensitive
eyes. It can also help remove
tear stains and reduce the
occurrence of tear stains with
regular use.

Inactive ingredients

Boric Acid, Sodium Borate,
Sodium Chloride, Sorbic Acid,
Disodium Edetate.

INSTRUCTIONS:

To flush eye:
Hold bottle tip over eye ond
gently squeeze bottle to
create a light, steady stream
of solution into the open eye
until debris is removed. Do not
touch eye.

For daily use against
allergens & irritation use
2-3 drops per eye daily. Do
not use in mouth of animal.
lndividuol results may vary.

WARNINGS AND PRECAUTIONS

For use on animals 12 weeks or older

CAUTION: FOR PET USE ONLY. NOT INTENDED
FOR HUMAN USE. Intended for external use
only. Keep out of reach of children and pets. In
case of accidental ingestion, contact a health care
professional immediately. If there is any irritation,
discontinue use and seek veterinary care.

00 NOT USE IF PRODUCT APPEARS TO BE
TAMPERED WITH OR SEAL IS BROKEN.

STORAGE AND HANDLING

STORE AT ROOM TEMPERATURE. DO NOT
EXPOSE TO EXCESSIVE HEAT OR MOISTURE.

Principal Display Panel

WELL&GOOD™
keep your pet well, for good

remove foreign objects, irritants, + tear stains

For Relief & Recovery

EYE RINSE & CLEANER FOR DOGS AND CATS 12 WEEKS+

FOR EMERGENCY & EVERYDAY USE
IDEAL FOR REMOVING FOREIGN
OBJECTS & IRRITANTS SUCH AS
POLLEN & DRIED MUCUS
HELPS REMOVE TEAR STAINS

4 FL OZ (118 ml)

Distributed by: International Pet Supplies and Distribution, Inc., San Diego, CA 92127

Contact us at 1.855.FAQ.Petco

©2022 Petco Animal Supplies, Inc.

All Rights Reserved. Made in China